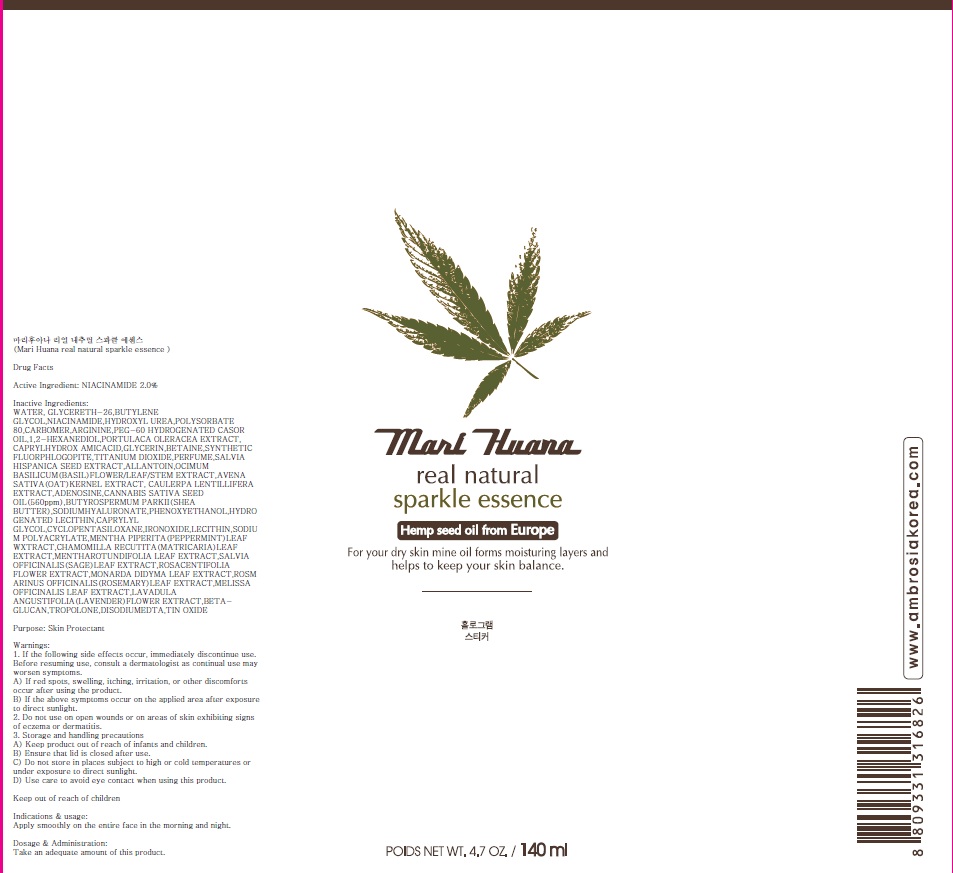 DRUG LABEL: Mari Huana Real Natural Sparkle Essence
NDC: 70603-040 | Form: CREAM
Manufacturer: JUNGLEFOOD CO., LTD.
Category: otc | Type: HUMAN OTC DRUG LABEL
Date: 20160520

ACTIVE INGREDIENTS: NIACINAMIDE 2.8 g/140 mL
INACTIVE INGREDIENTS: WATER; GLYCERETH-26

ACTIVE INGREDIENT

Active Ingredient: NIACINAMIDE 2.0%

INACTIVE INGREDIENT

Inactive Ingredients: WATER, GLYCERETH-26,BUTYLENE GLYCOL,NIACINAMIDE,HYDROXYL UREA,POLYSORBATE 80,CARBOMER,ARGININE,PEG-60 HYDROGENATED CASOR OIL,1,2-HEXANEDIOL,PORTULACA OLERACEA EXTRACT, CAPRYLHYDROX AMICACID,GLYCERIN,BETAINE,SYNTHETIC FLUORPHLOGOPITE,TITANIUM DIOXIDE,PERFUME,SALVIA HISPANICA SEED EXTRACT,ALLANTOIN,OCIMUM BASILICUM(BASIL)FLOWER/LEAF/STEM EXTRACT,AVENA SATIVA(OAT)KERNEL EXTRACT, CAULERPA LENTILLIFERA EXTRACT,ADENOSINE,CANNABIS SATIVA SEED OIL(560ppm),BUTYROSPERMUM PARKII(SHEA BUTTER),SODIUMHYALURONATE,PHENOXYETHANOL,HYDRO GENATED LECITHIN,CAPRYLYL GLYCOL,CYCLOPENTASILOXANE,IRONOXIDE,LECITHIN,SODIU M POLYACRYLATE,MENTHA PIPERITA(PEPPERMINT)LEAF WXTRACT,CHAMOMILLA RECUTITA(MATRICARIA)LEAF EXTRACT,MENTHAROTUNDIFOLIA LEAF EXTRACT,SALVIA OFFICINALIS(SAGE)LEAF EXTRACT,ROSACENTIFOLIA FLOWER EXTRACT,MONARDA DIDYMA LEAF EXTRACT,ROSM ARINUS OFFICINALIS(ROSEMARY)LEAF EXTRACT,MELISSA OFFICINALIS LEAF EXTRACT,LAVADULA ANGUSTIFOLIA(LAVENDER)FLOWER EXTRACT,BETAGLUCAN, TROPOLONE,DISODIUMEDTA,TIN OXIDE

PURPOSE

Purpose: Skin Protectant

WARNINGS

Warnings: 1. If the following side effects occur, immediately discontinue use. Before resuming use, consult a dermatologist as continual use may worsen symptoms. A) If red spots, swelling, itching, irritation, or other discomforts occur after using the product. B) If the above symptoms occur on the applied area after exposure to direct sunlight. 2. Do not use on open wounds or on areas of skin exhibiting signs of eczema or dermatitis. 3. Storage and handling precautions A) Keep product out of reach of infants and children. B) Ensure that lid is closed after use. C) Do not store in places subject to high or cold temperatures or under exposure to direct sunlight. D) Use care to avoid eye contact when using this product. Keep out of reach of children

KEEP OUT OF REACH OF CHILDREN

INDICATIONS & USAGE

Indications & usage: Apply smoothly on the entire face in the morning and night.

DOSAGE & ADMINISTRATION

Dosage & Administration: Take an adequate amount of this product.